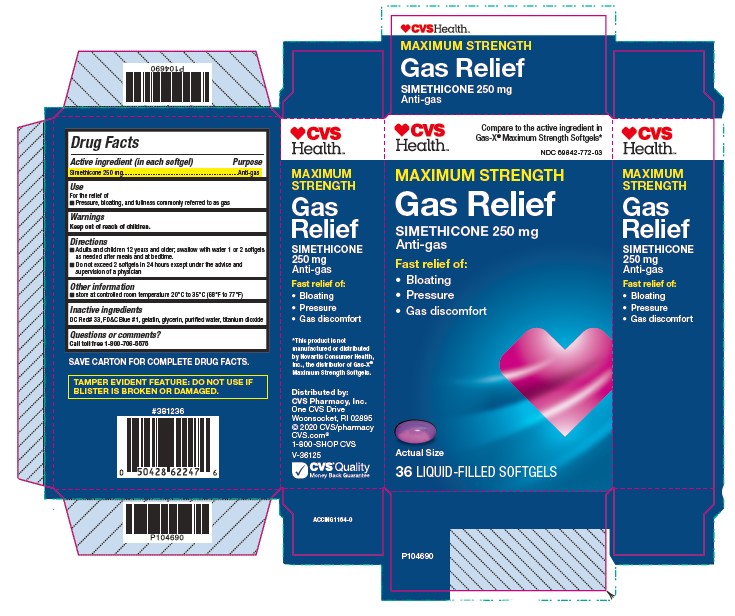 DRUG LABEL: Gas Relief
NDC: 69842-772 | Form: CAPSULE, GELATIN COATED
Manufacturer: CVS Pharmacy
Category: otc | Type: HUMAN OTC DRUG LABEL
Date: 20200513

ACTIVE INGREDIENTS: DIMETHICONE 250 mg/1 1
INACTIVE INGREDIENTS: D&C RED NO. 33; WATER; GELATIN, UNSPECIFIED; FD&C BLUE NO. 1; GLYCERIN; TITANIUM DIOXIDE

Drug Facts

Active Ingredient

(in each softgel)

Simethicone 250mg

Purpose

Anti-gas

Use

For the relief of

- Pressure, bloating or fullness commonly referred to as gas

Directions

- Adults and children 12 years and older; swallow with water 1 or 2 softgels as needed after meals and at bedtime.
- Do not exceed 2 softgels in 24 hours except under the advice and supervision of a physician

Other Information

- store at room temperature 20ºC to 35ºC (68ºF to 77ºF)

Inactive Ingredients

DC Red # 33, FD&C Blue No. 1, Gelatin, Glycerin, purified water, titanium dioxide

Questions or comments?

Call toll-free 1-800-706-5575

Principal Display Panel

CVS Maximum Strength

Gas Relief

Simethicone 250 mg (anti-gas)

36 Liquid Filled Softgels

Blister Carton label

NDC# 69842-772-03

Simethicone Maximum Strength Softgels are concentrated to contain liquid gas-fighting medicine in a small softgel so they are easy to swallow, and there is no chalky taste.